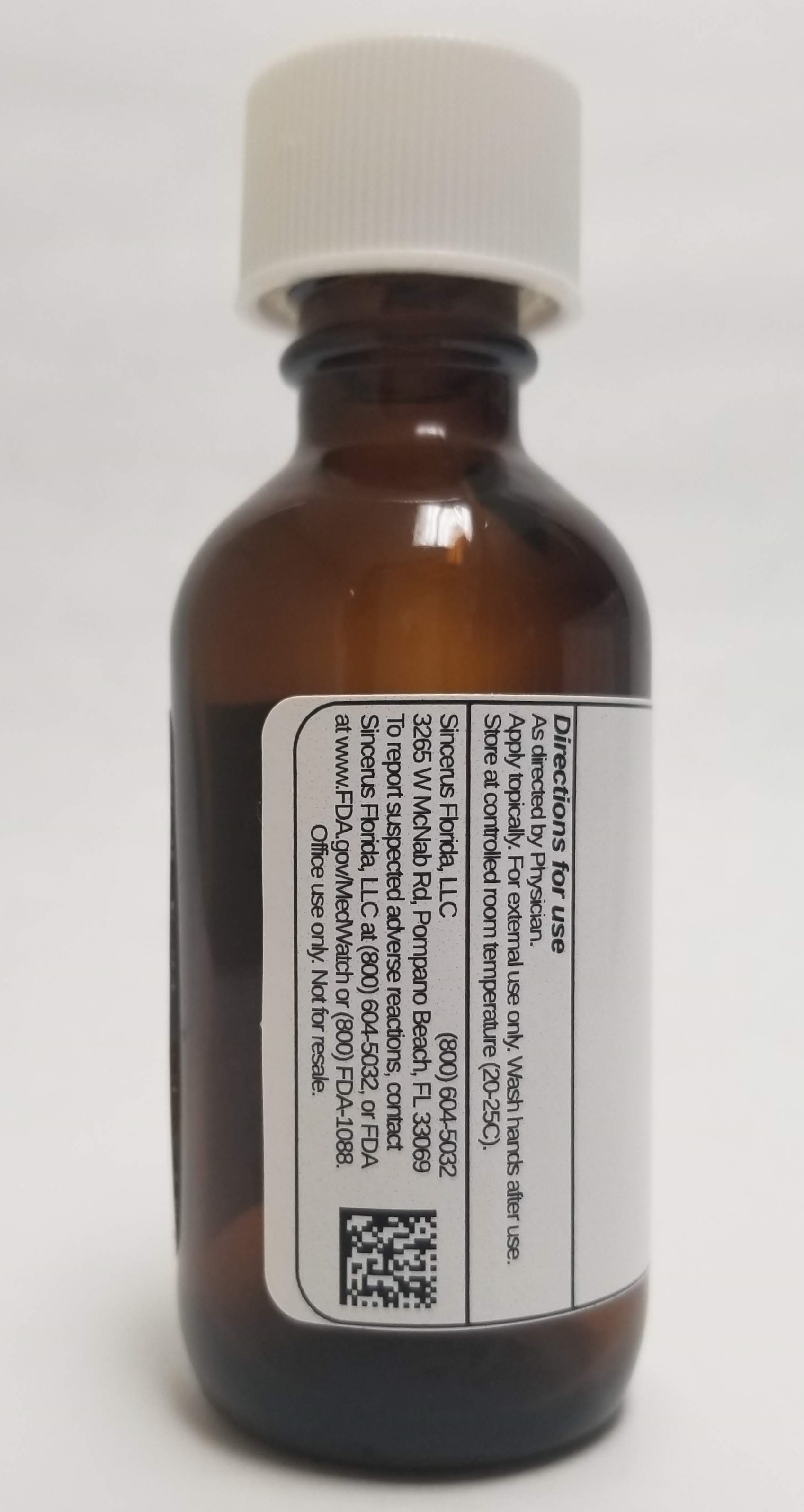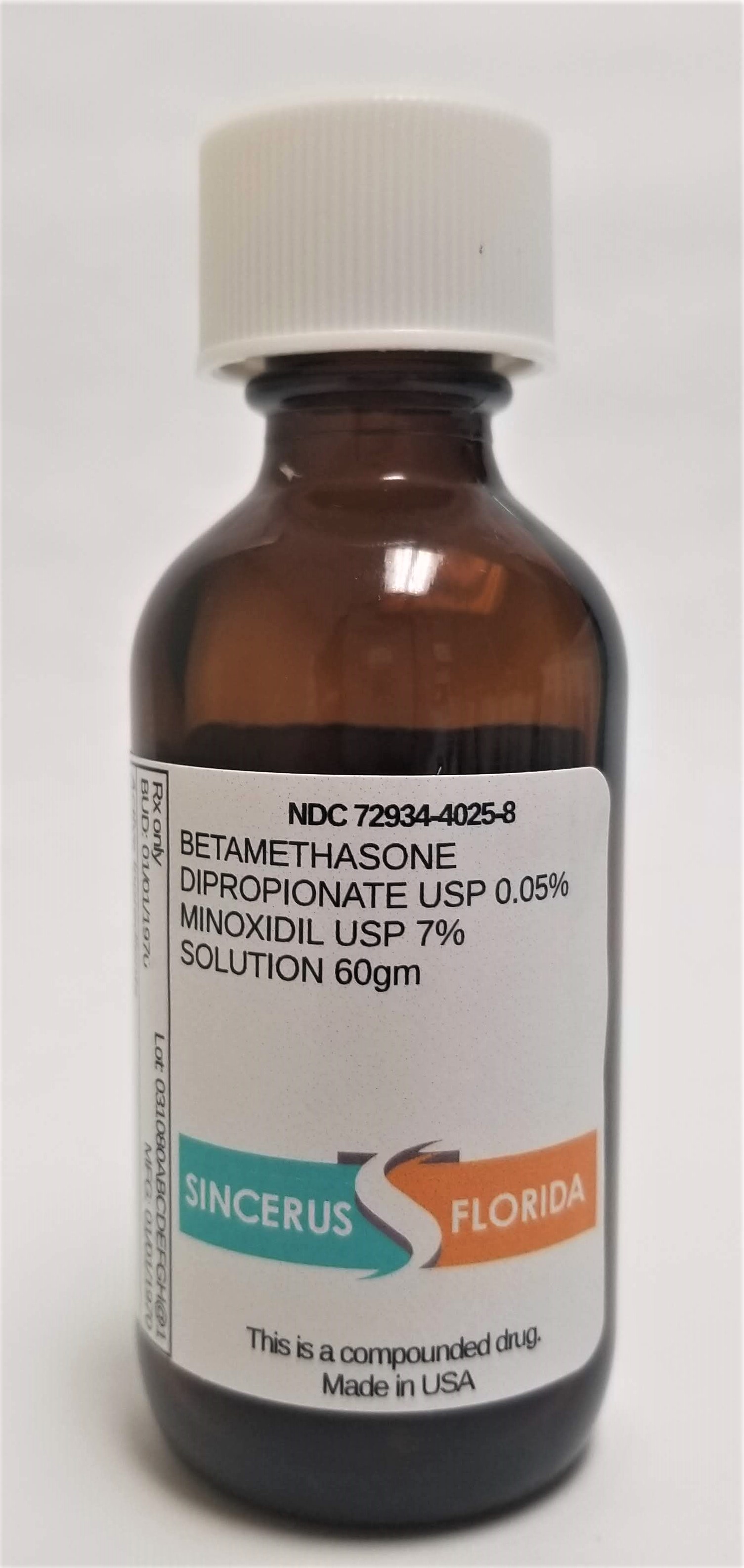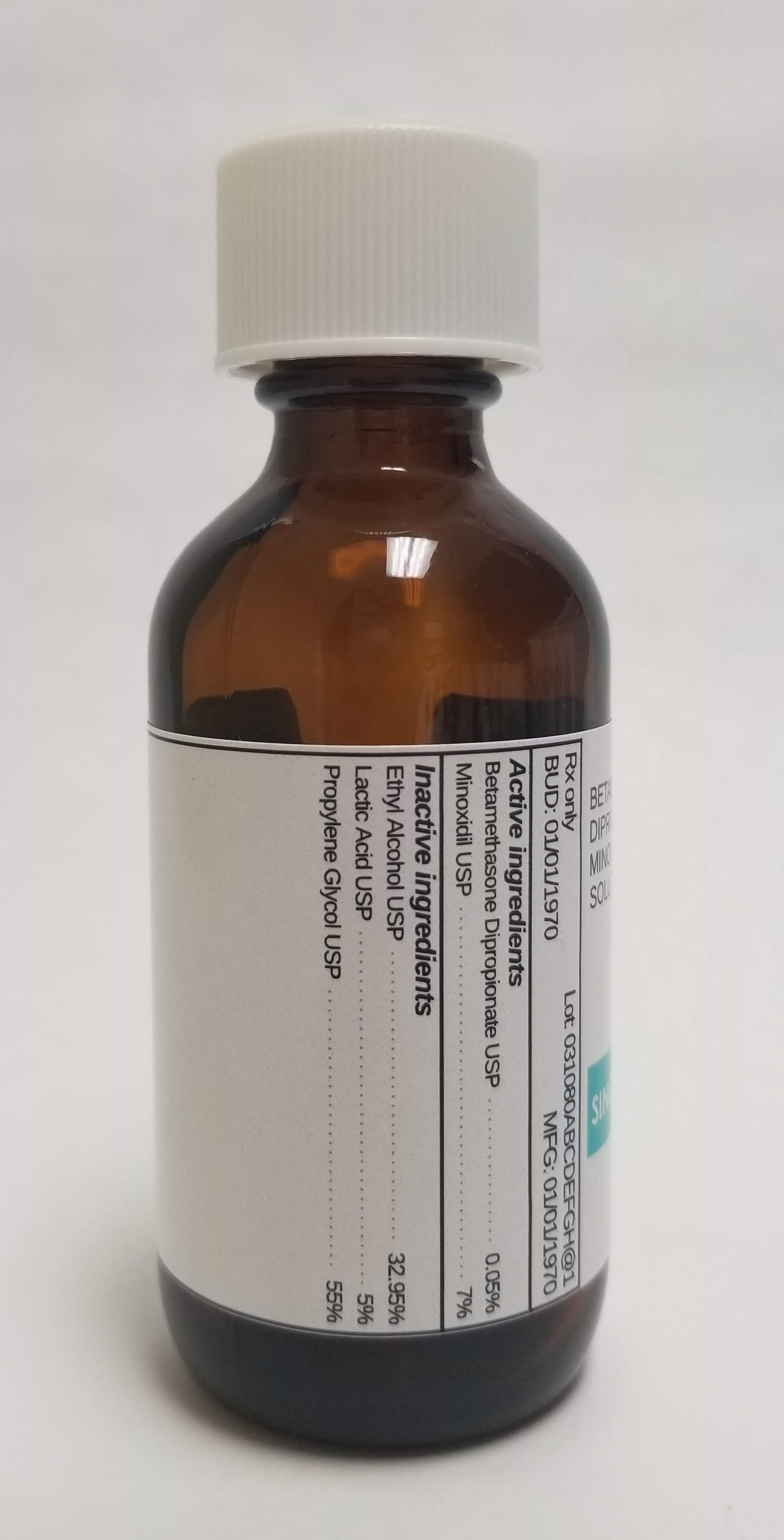 DRUG LABEL: BETAMETHASONE DIPROPRIONATE 0.05% / MINOXIDIL 7%
NDC: 72934-4025 | Form: SOLUTION
Manufacturer: Sincerus Florida, LLC
Category: prescription | Type: HUMAN PRESCRIPTION DRUG LABEL
Date: 20190509

ACTIVE INGREDIENTS: BETAMETHASONE DIPROPIONATE 0.05 g/100 g; MINOXIDIL 7 g/100 g

BETAMETHASONE DIPROPRIONATE 0.05% / MINOXIDIL 7%